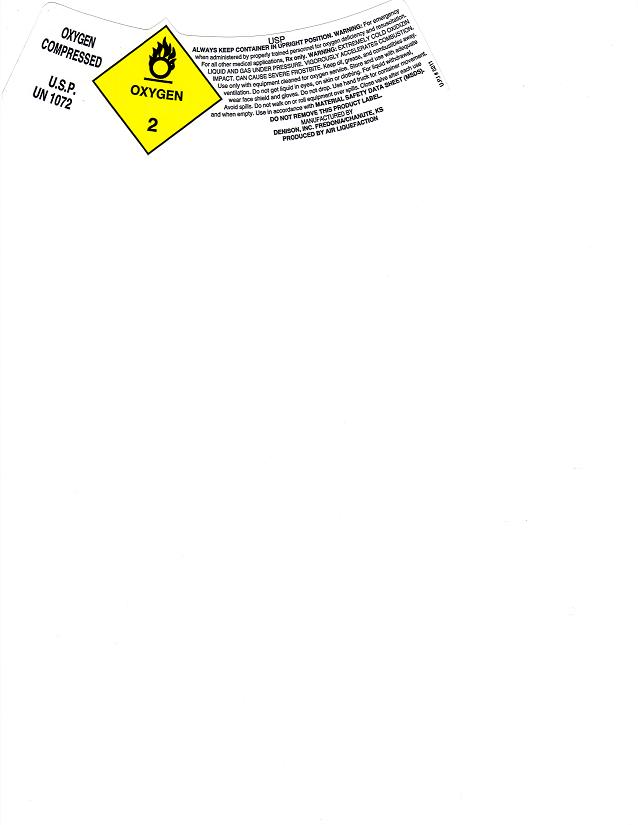 DRUG LABEL: Oxygen
NDC: 24913-2234 | Form: GAS
Manufacturer: DENISON INC
Category: prescription | Type: HUMAN PRESCRIPTION DRUG LABEL
Date: 20100730

ACTIVE INGREDIENTS: OXYGEN 990 mL/1 L

Oxygen Shoulder Label